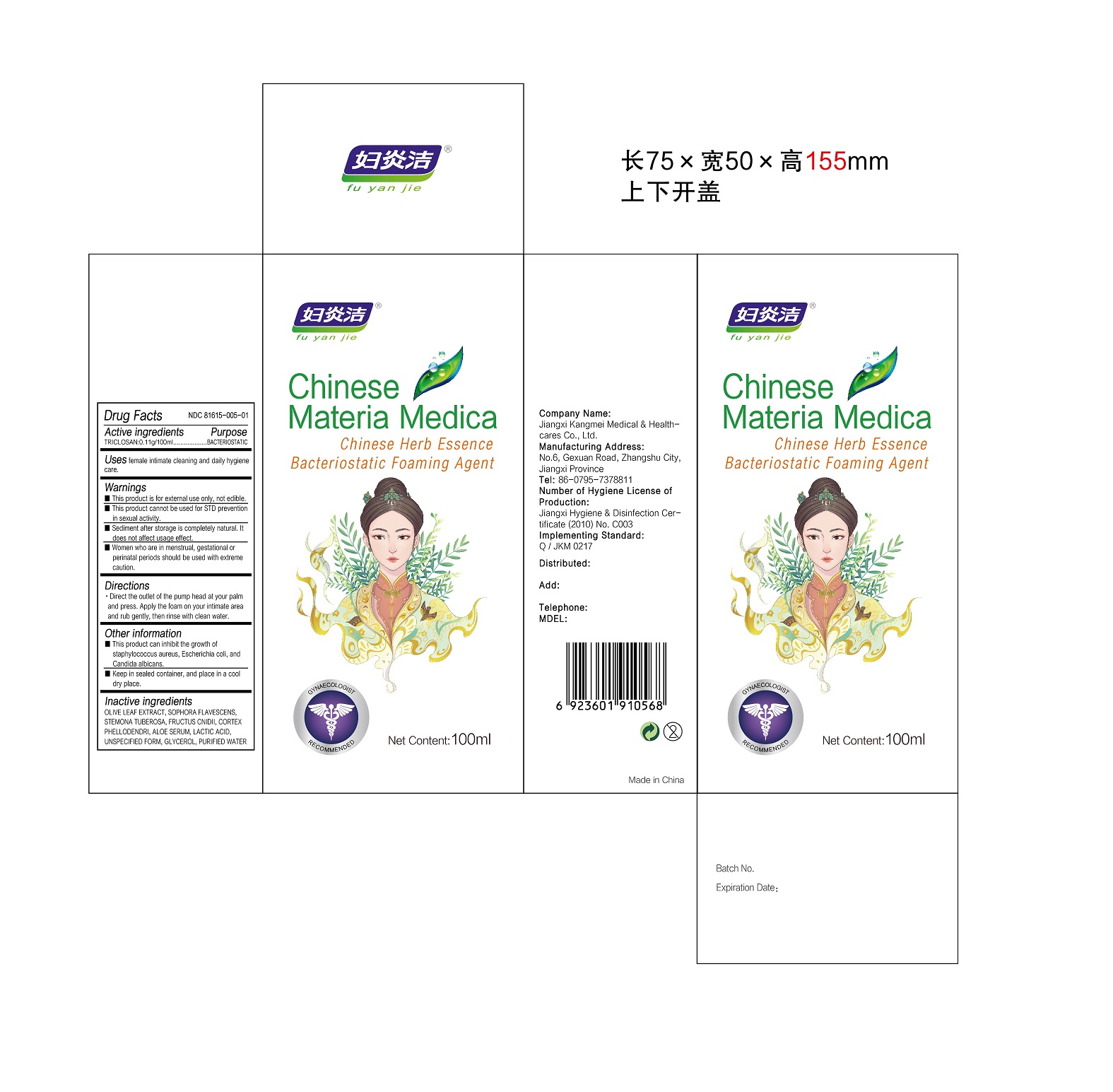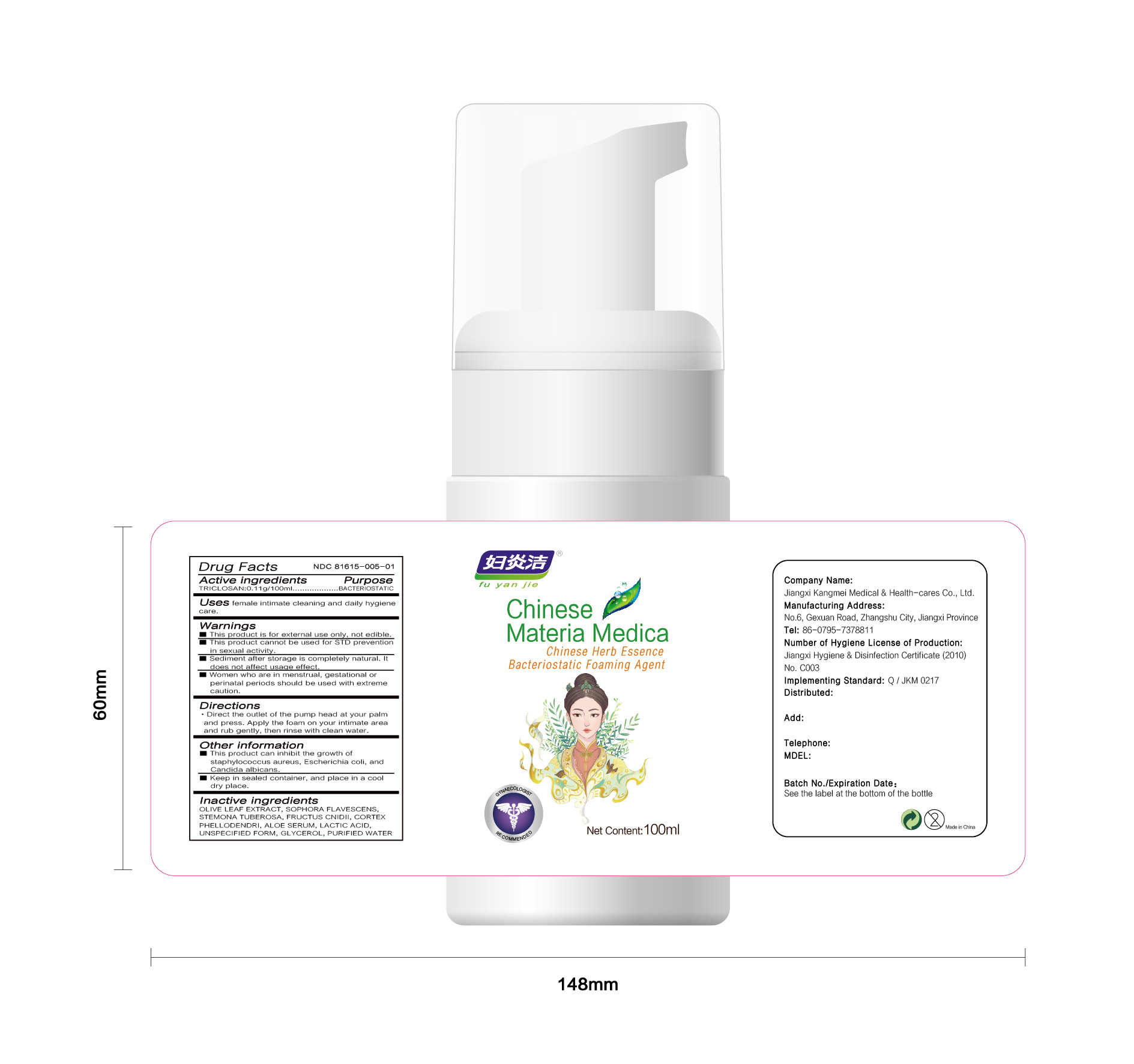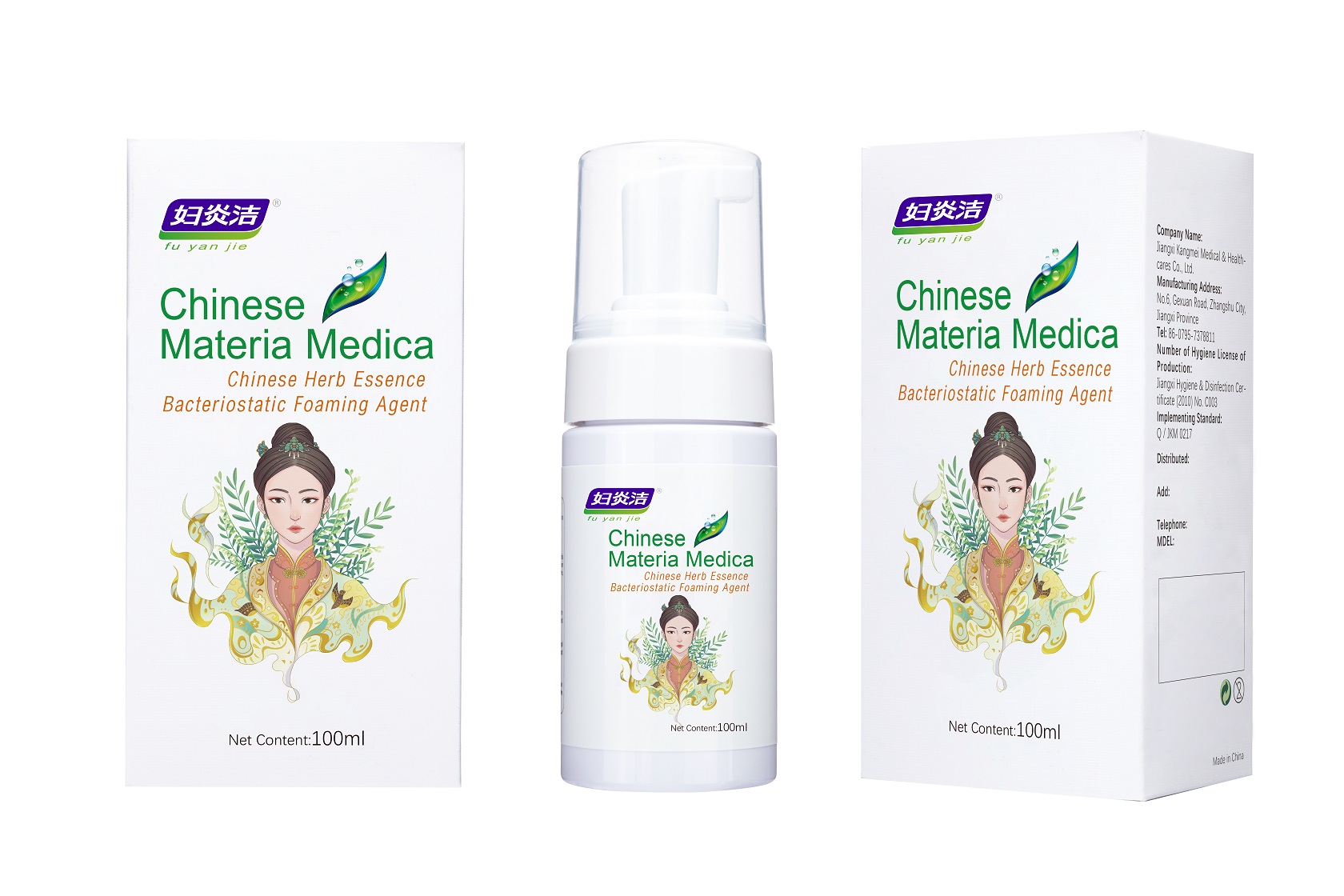 DRUG LABEL: CHINESE HERB ESSENCE BACTERIOSTATIC FOAMING AGENT
NDC: 81615-005 | Form: LIQUID
Manufacturer: Jiangxi Renhetang pharmaceutical chain Co., Ltd.
Category: otc | Type: HUMAN OTC DRUG LABEL
Date: 20210420

ACTIVE INGREDIENTS: TRICLOSAN 0.11 g/100 mL
INACTIVE INGREDIENTS: OSTHOL; SOPHORA FLAVESCENS ROOT; STEMONA TUBEROSA ROOT; WATER; PHELLODENDRON CHINENSE WHOLE; ALOE VERA LEAF; LACTIC ACID, UNSPECIFIED FORM; GLYCERIN; OLEA EUROPAEA LEAF

CHINESE HERB ESSENCE BACTERIOSTATIC FOAMING AGENT

CHINESE HERB ESSENCE BACTERIOSTATIC FOAMING AGENT

Active Ingredient(s)

TRICLOSAN 0.11g/100mL

Purpose

BACTERIOSTATIC

Use

Uses female intimate cleaning and daily hygiene care.

Warnings

This product is for external use only, not edible.

This product cannot be used for STD prevention in sexual activity.

Sediment after storage is completely natural. It does not affect usage effect.

Women who are in menstrual, gestational or perinatal periods should be used with extreme caution.

When using this product keep out of eyes, ears, and mouth. In case of contact with eyes, rinse eyes thoroughly with water.
Stop use and ask a doctor if irritation or rash occurs. These may be signs of a serious condition.
Keep out of reach of children. If swallowed, get medical help or contact a Poison Control Center right away.

Stop use and ask a doctor if irritation or rash occurs. These may be signs of a serious condition.

Keep out of reach of children. If swallowed, get medical help or contact a Poison Control Center right away.

Directions

Direct the outlet of the pump head at your palm and press. Apply the foam on your intimate area and rub gently, then rinse with clean water.

Other information

This product can inhibit the growth of staphylococcus aureus, Escherichia coli, and Candida albicans.

Keep in sealed container, and place in a cool dry place.

Inactive ingredients

OLIVE LEAF EXTRACT,SOPHORA FLAVESCENS,STEMONA TUBEROSA, FRUCTUS CNIDII,CORTEX PHELLODENDRI,ALOE SERUM, LACTIC ACID, UNSPECIFIED FORM, GLYCEROL, PURIFIED WATER